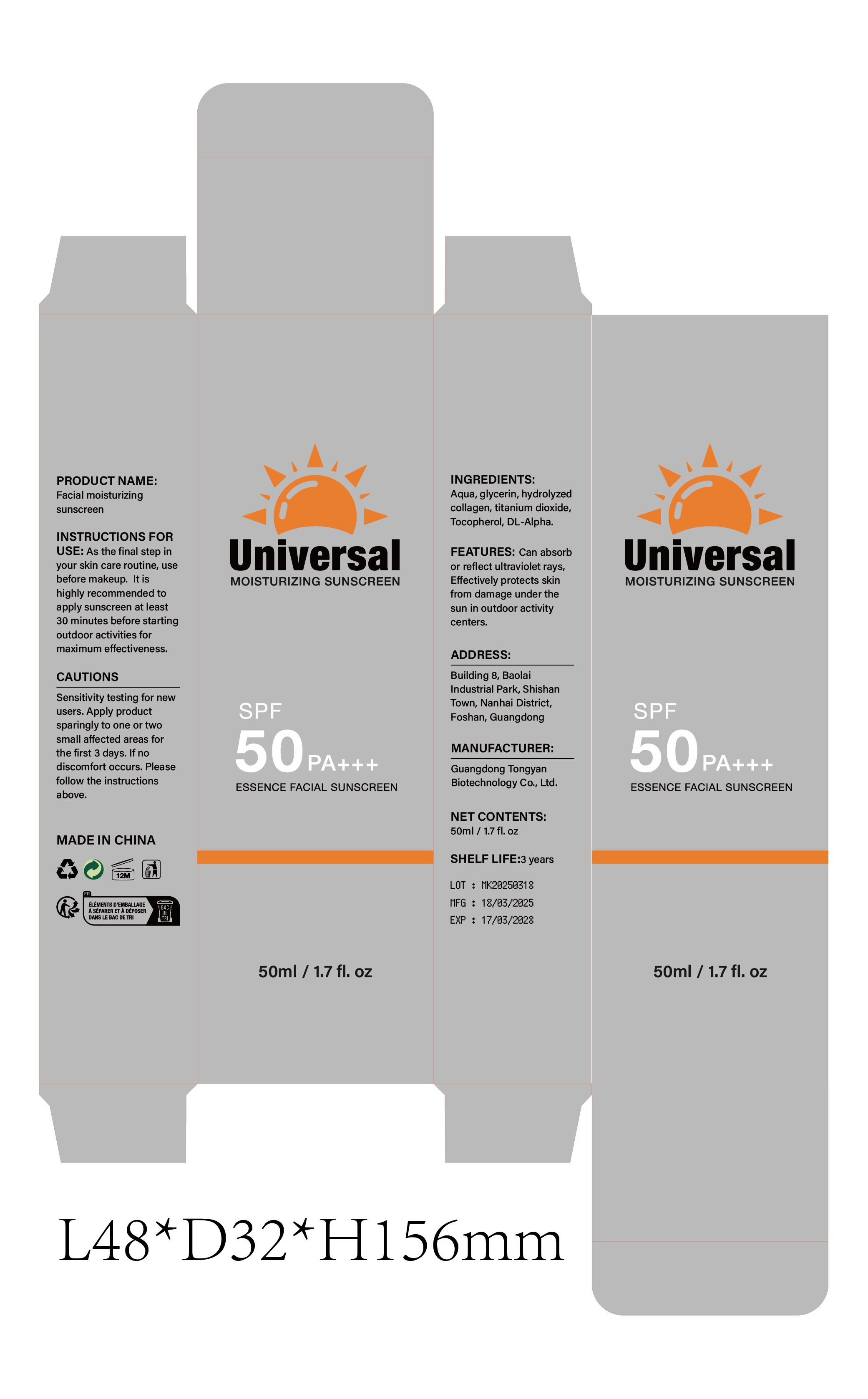 DRUG LABEL: Facial moisturizing sunscreen
NDC: 85594-004 | Form: CREAM
Manufacturer: Dongguan Haiyi Cosmetics Co., Ltd.
Category: otc | Type: HUMAN OTC DRUG LABEL
Date: 20250511

ACTIVE INGREDIENTS: TITANIUM DIOXIDE 5 mg/100 mL
INACTIVE INGREDIENTS: HYDROLYZED PORCINE COLLAGEN (ENZYMATIC; 3000 MW); TOCOPHEROL; GLYCERIN; .ALPHA.-TOCOPHEROL, DL-; AQUA

85594-004-01 Facial moisturizing sunscreen

ACTIVE INGREDIENT

Titanium Dioxide

INACTIVE INGREDIENT

Aqua，Glycerin，Hydrolyzed Collagen，Tocopherol，DL-Alpha

PURPOSE

Apply an adequate amount (about a coin-sized portion or 2mg/cm²) evenly to the face and neck.

WARNINGS

Sensitivity testing for new users. Apply product sparingly to one or twosmall affected areas forthe first 3 days. lf no discomfort occurs. Please follow the instructions above.

STOP USE

his product may cause allergic reactions in asmall number of people.
lf you experience any discomfort,please stop using it immediately.

DO NOT USE

Not suitable for use by children, pregnantor breast feeding people.

KEEP OUT OF REACH OF CHILDREN

KEEP THE PRODUCT OUT OF REACH OF CHILDREN to

INDICATIONS AND USAGE

As the final step inyour skin care routine, use before makeup. lt is highly recommended to apply sunscreen at least30 minutes before starting outdoor activities for maximum effectiveness.

DOSAGE AND ADMINISTRATION

Apply an adequate amount (about a coin-sized portion or 2mg/cm²) evenly to the face and neck.